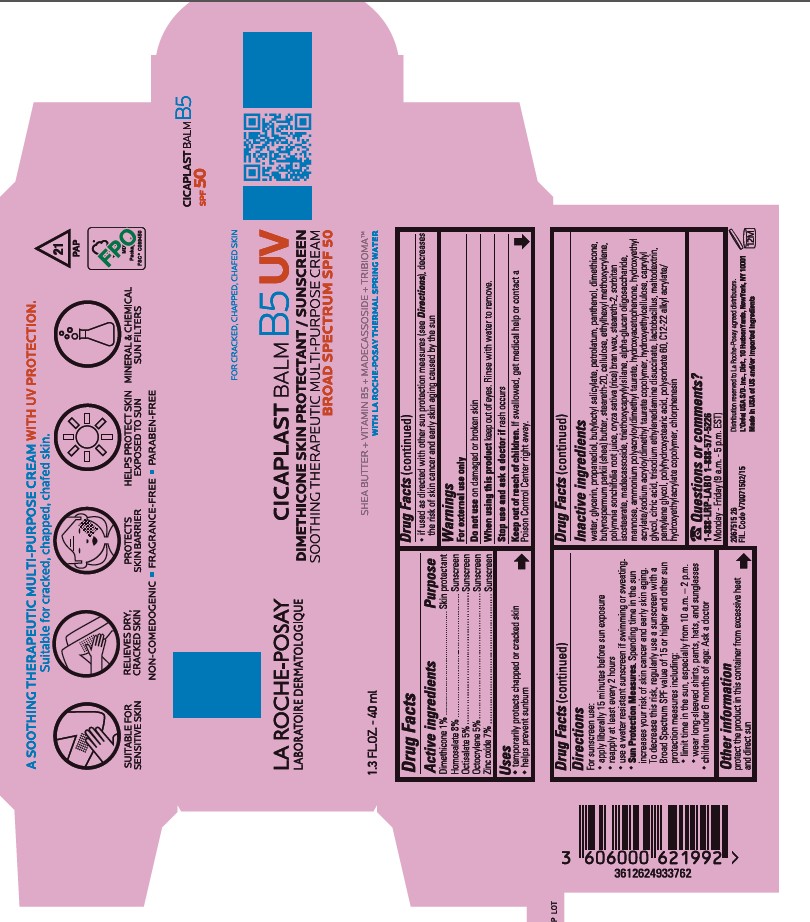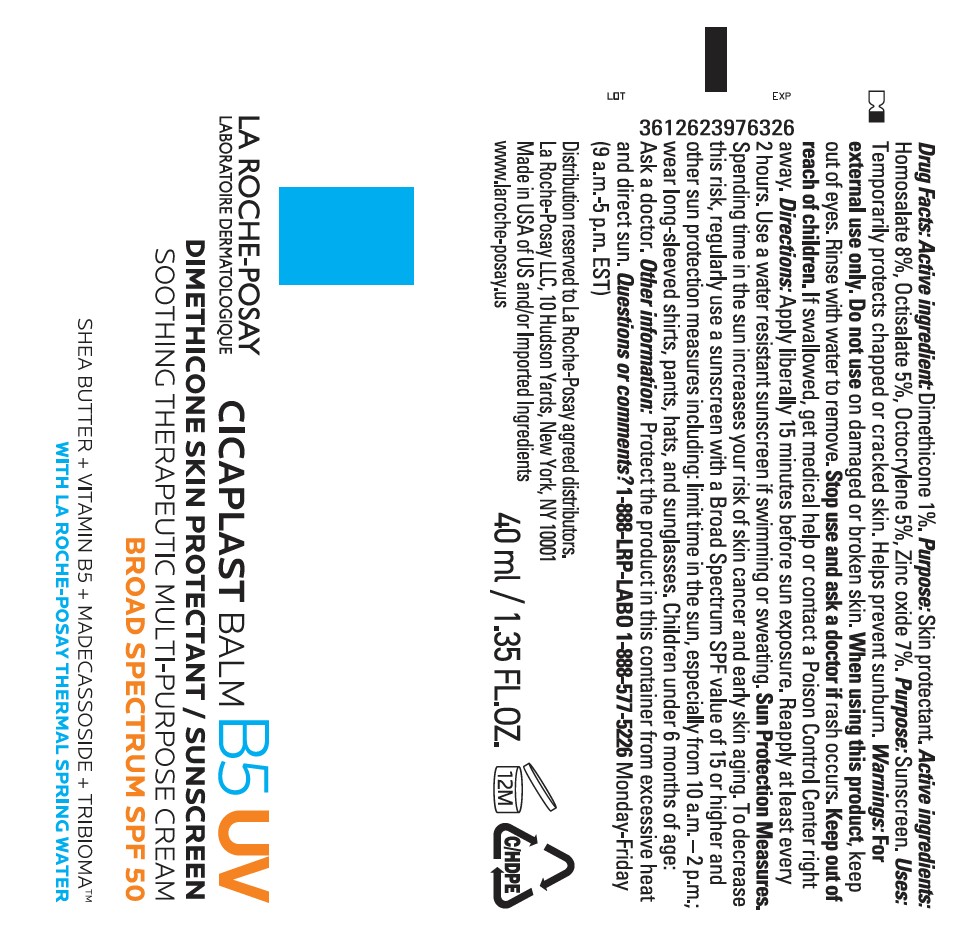 DRUG LABEL: LA ROCHE POSAY Laboratoire Dermatologique Cicaplast Balm B5 UV Skin Protectant Sunscreen Soothing Therapeutic Multi-Purpose Broad Spectrum SPF 50
NDC: 82046-992 | Form: CREAM
Manufacturer: L’Oreal USA Products Inc
Category: otc | Type: HUMAN OTC DRUG LABEL
Date: 20251205

ACTIVE INGREDIENTS: HOMOSALATE 80 mg/1 mL; OCTISALATE 50 mg/1 mL; DIMETHICONE 10 mg/1 mL; OCTOCRYLENE 50 mg/1 mL; ZINC OXIDE 70 mg/1 mL
INACTIVE INGREDIENTS: WATER; GLYCERIN; PROPANEDIOL; BUTYLOCTYL SALICYLATE; PETROLATUM; PANTHENOL; BUTYROSPERMUM PARKII (SHEA) BUTTER; STEARETH-20; POWDERED CELLULOSE; ETHYLHEXYL METHOXYCRYLENE; POLYMNIA SONCHIFOLIA ROOT JUICE; ORYZA SATIVA (RICE) BRAN; STEARETH-2; SORBITAN ISOSTEARATE; MADECASSOSIDE; TRIETHOXYCAPRYLYLSILANE; ALPHA-GLUCAN OLIGOSACCHARIDE; MANNOSE; AMMONIUM POLYACRYLOYLDIMETHYL TAURATE; HYDROXYACETOPHENONE; HYDROXYETHYL ACRYLATE/SODIUM ACRYLOYLDIMETHYL TAURATE COPOLYMER (100000 MPA.S AT 1.5%); HYDROXYETHYLCELLULOSE; CAPRYLYL GLYCOL; CITRIC ACID; TRISODIUM ETHYLENEDIAMINE DISUCCINATE; LACTOBACILLUS; MALTODEXTRIN; PENTYLENE GLYCOL; POLYHYDROXYSTEARIC ACID STEARATE; POLYSORBATE 60; CHLORPHENESIN

Drug Facts

Active ingredients

Dimethicone 1%

Homosalate 8%

Octisalate 5%

Octocrylene 5%

Zinc oxide 7%

Purpose

Skin protectant

Sunscreen

Sunscreen

Sunscreen

Sunscreen

Uses

- temporarily protects chapped or cracked skin
- helps prevent sunburn
- if used as directed with other sun protection measures (see Directions), decreases the risk of skin cancer and early skin aging caused by the sun

Warnings

For external use only

Do not use

on damaged or broken skin

When using this product

keep out of eyes. Rinse with water to remove.

Stop use and ask a doctor if

rash occurs

Keep out of reach of children.

If swallowed, get medical help or contact a Poison Control Center right away.

Directions

For sunscreen use:

- apply liberally 15 minutes before sun exposure
- reapply at least every 2 hours
- use a water resistant sunscreen if swimming or sweating.
- Sun Protection Measures. Spending time in the sun increases your risk of skin cancer and early skin aging. To decrease this risk, regularly use a sunscreen with a Broad Spectrum SPF value of 15 or higher and other sun protection measures including:
- limit time in the sun, especially from 10 a.m. – 2 p.m.
- wear long-sleeved shirts, pants, hats, and sunglasses
- children under 6 months of age: Ask a doctor

Other information

- protect the product in this container from excessive heat and direct sun

Inactive ingredients

water, glycerin, propanediol, butyloctyl salicylate, petrolatum, panthenol, dimethicone, butyrospermum parkii (shea) butter, steareth-20, cellulose, ethylhexyl methoxycrylene, polymnia sonchifolia root juice, oryza sativa (rice) bran wax, steareth-2, sorbitan isostearate, madecassoside, triethoxycaprylylsilane, alpha-glucan oligosaccharide, mannose, ammonium polyacryloyldimethyl taurate, hydroxyacetophenone, hydroxyethyl acrylate/sodium acryloyldimethyl taurate copolymer, hydroxyethylcellulose, caprylyl glycol, citric acid, trisodium ethylenediamine disuccinate, lactobacillus, maltodextrin, pentylene glycol, polyhydroxystearic acid, polysorbate 60, C12-22 alkyl acrylate/hydroxyethyl acrylate copolymer, chlorphenesin

Questions or comments?

1-888-LRP-LABO 1-888-577-5226

Monday - Friday (9 a.m. - 5 p.m. EST)